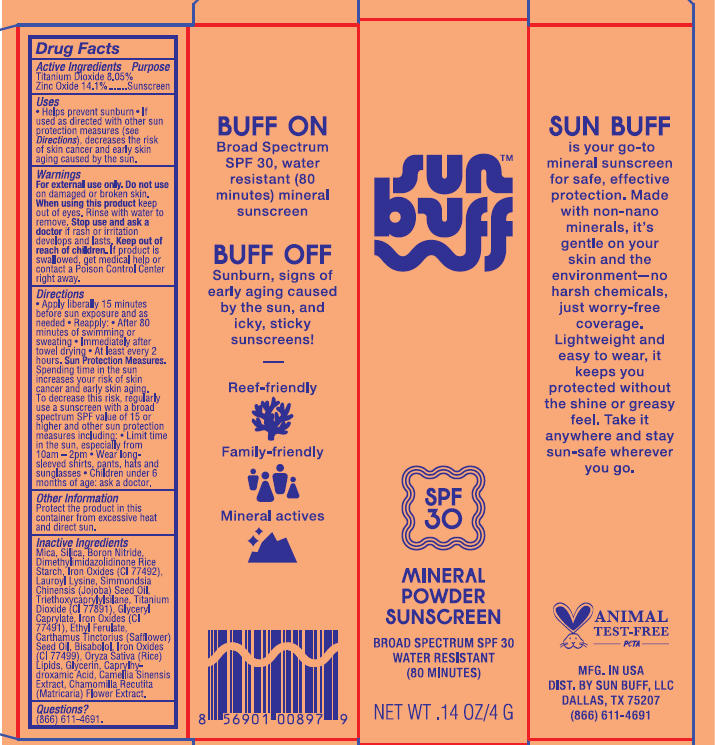 DRUG LABEL: SUN BUFF SPF 30 MINERAL SUNSCREEN
NDC: 58274-030 | Form: POWDER
Manufacturer: SPF Ventures, LLC
Category: otc | Type: HUMAN OTC DRUG LABEL
Date: 20250924

ACTIVE INGREDIENTS: TITANIUM DIOXIDE 8.05 g/100 g; ZINC OXIDE 14.1 g/100 g
INACTIVE INGREDIENTS: BORON NITRIDE; CHAMOMILE; CAMELLIA SINENSIS LEAF; SILICA; CARTHAMUS TINCTORIUS (SAFFLOWER) SEED OIL; BISABOLOL; GLYCERIN; LAUROYL LYSINE; CI 77499; GLYCERYL CAPRYLATE; ETHYL FERULATE; DIMETHYLIMIDAZOLIDINONE RICE STARCH; CI 77492; RICE BRAN OIL; SIMMONDSIA CHINENSIS (JOJOBA) SEED OIL; MICA; CI 77491; TRIETHOXYCAPRYLYLSILANE; CAPRYLHYDROXAMIC ACID

SUN BUFF SPF 30 MINERAL POWDER SUNSCREEN

Active ingredients

ZINC OXIDE 14.1%

TITANIUM DIOXIDE 8.05%

Purpose

Sunscreen

Uses

- Helps prevent sunburn
- If used as directed with other sun protection measures (see Directions), decreases the risk of skin cancer and early skin aging caused by the sun.

Warnings

For external use only.

Do not use on damaged or broken skin.

When using this product keep out of eyes. Rinse with water to remove.

Stop use and ask a doctor if rash or irritation develops and lasts.

Keep out of reach of children

If product is swallowed, get medical help or contact a Poison Control Center right away.

Directions

- Apply liberally 15 minutes before sub exposure and as needed
- Reapply: After 80 minutes of swimming or sweating; Immediately after towel drying; At least every 2 hours

Sub Protection Measures.

Spending time in the sun increases your risk of skin cancer and early skin aging. To decrease this risk, regularly use a sunscreen with a broad spectrum SPF value of 15 or higher and other sun protection measures including: Limit time in the sun, especially from 10am-2pm; Wear long-sleeved shirts, pants, hats and sunglasses;

- Children under 6 months of age: ask a doctor

Other Information

Protect the product in this container from excessive heat and direct sun.

Inactive ingredients

MICA

SILICA

BORON NITRIDE

DIMETHYLIMIDAZOLIDINONE RICE STARCH

IRON OXIDES (CI 77492)

LAUROYL LYSINE

SIMMONDSIA CHINENSIS (JOJOBA) SEED OIL

TRIETHOXYCAPRYLYLSILANE

TITANIUM DIOXIDE (CI 77981)

GLYCERYL CAPRYLATE

IRON OXIDES (CI 77491)

ETHYL FERULATE

CARTHAMUS TINCTORIUS (SAFFLOWER) SEED OIL

BISABOLOL

IRON OXIDES (CI 77499)

ORYZA SATIVA (RICE) LIPIDS

GLYCERIN

CAPRYLHYDROXAMIC ACID

CAMELLIA SINENSIS EXTRACT

CHAMOMILLA RECUTITA (MATRICARIA) FLOWER EXTRACT